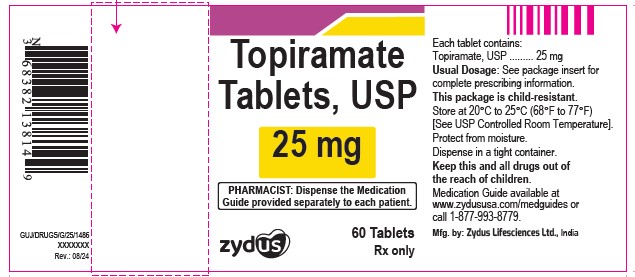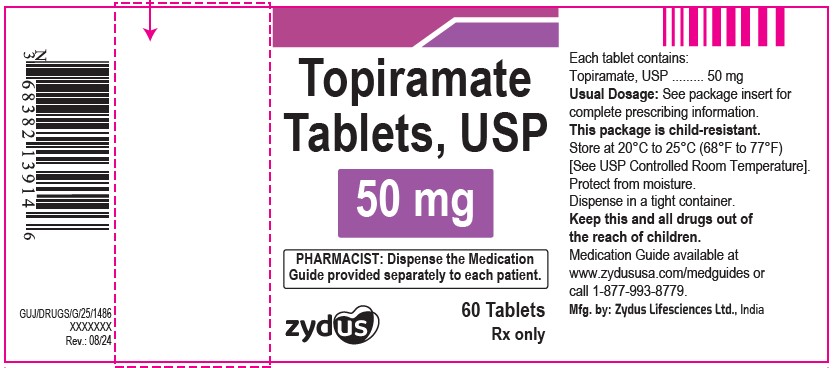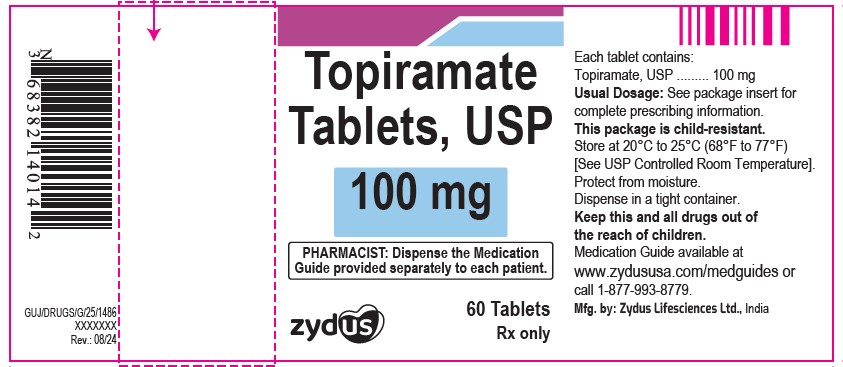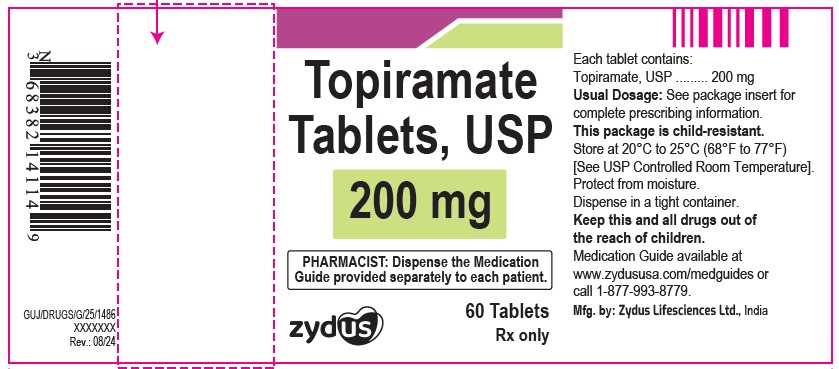 DRUG LABEL: topiramate
NDC: 65841-647 | Form: TABLET, FILM COATED
Manufacturer: Zydus Lifesciences Limited
Category: prescription | Type: HUMAN PRESCRIPTION DRUG LABEL
Date: 20240814

ACTIVE INGREDIENTS: TOPIRAMATE 25 mg/1 1
INACTIVE INGREDIENTS: HYPROMELLOSES; MAGNESIUM STEARATE; POLYETHYLENE GLYCOL, UNSPECIFIED; SODIUM STARCH GLYCOLATE TYPE A POTATO; TALC; TITANIUM DIOXIDE; SILICON DIOXIDE; CELLULOSE, MICROCRYSTALLINE; ANHYDROUS LACTOSE

TOPIRAMATE TABLETS and TOPIRAMATE CAPSULES

PACKAGE LABEL.PRINCIPAL DISPLAY PANEL

NDC 65841-647-14 in bottle of 60 tablets

Topiramate Tablets USP, 25 mg

60 tablets

Rx only

NDC 65841-648-14 in bottle of 60 tablets

Topiramate Tablets USP, 50 mg

60 tablets

Rx only

NDC 65841-649-14 in bottle of 60 tablets

Topiramate Tablets USP, 100 mg

60 tablets

Rx only

NDC 65841-650-14 in bottle of 60 tablets

Topiramate Tablets USP, 200 mg

60 tablets

Rx only